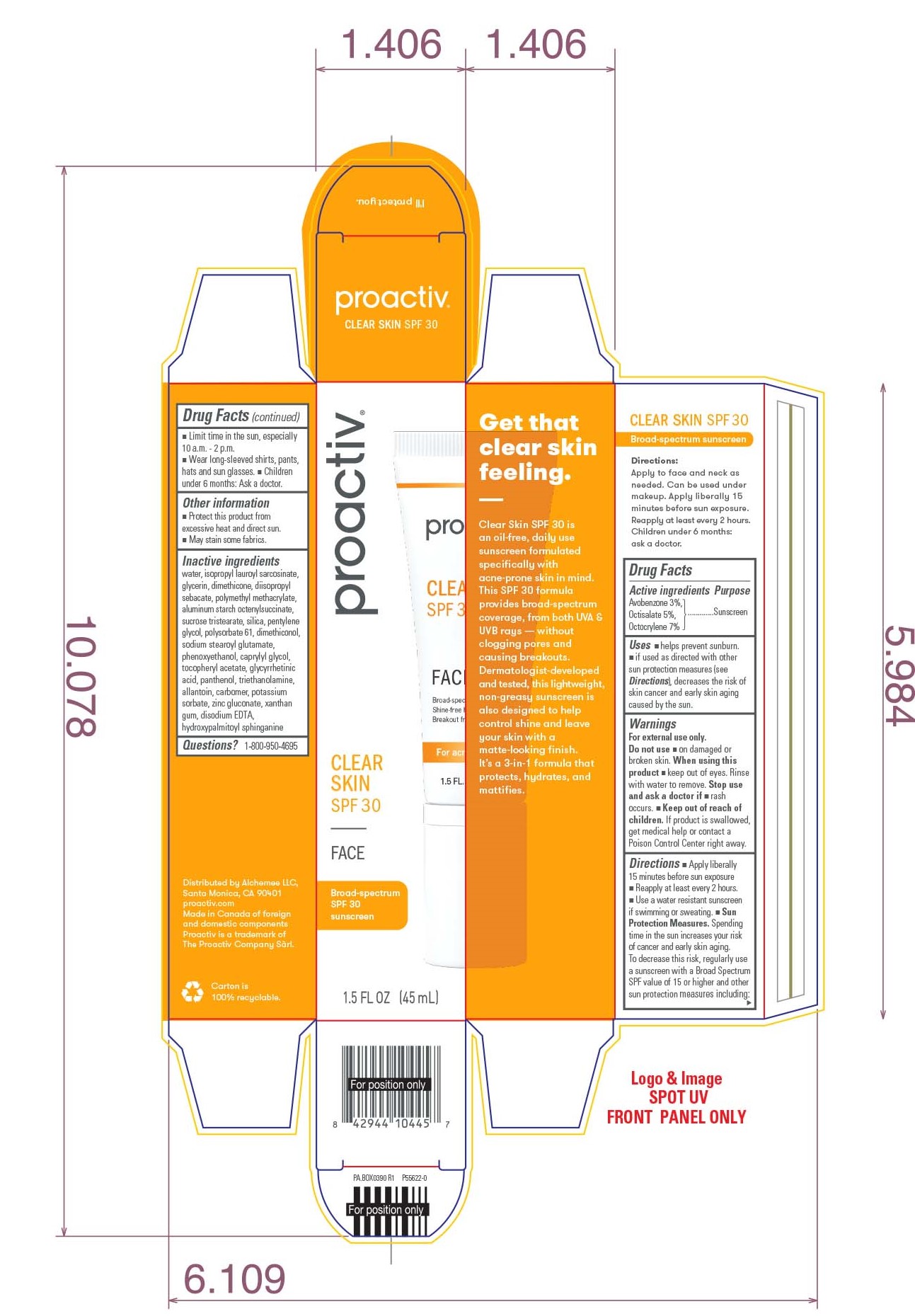 DRUG LABEL: Proactiv Clear Skin SPF 30
NDC: 11410-073 | Form: LOTION
Manufacturer: Alchemee, LLC
Category: otc | Type: HUMAN OTC DRUG LABEL
Date: 20260107

ACTIVE INGREDIENTS: AVOBENZONE 3 mg/100 mL; OCTISALATE 5 mg/100 mL; OCTOCRYLENE 7 mg/100 mL
INACTIVE INGREDIENTS: WATER; ISOPROPYL LAUROYL SARCOSINATE; GLYCERIN; DIMETHICONE; DIISOPROPYL SEBACATE; POLY(METHYL METHACRYLATE; 450000 MW); ALUMINUM STARCH OCTENYLSUCCINATE; SUCROSE TRISTEARATE; SILICON DIOXIDE; PENTYLENE GLYCOL; POLYSORBATE 61; SODIUM STEAROYL GLUTAMATE; PHENOXYETHANOL; CAPRYLYL GLYCOL; .ALPHA.-TOCOPHEROL ACETATE; ENOXOLONE; PANTHENOL; TROLAMINE; ALLANTOIN; CARBOXYPOLYMETHYLENE; POTASSIUM SORBATE; ZINC GLUCONATE; XANTHAN GUM; EDETATE DISODIUM ANHYDROUS; HYDROXYPALMITOYL SPHINGANINE

Proactiv® Clear Skin SPF 30

Drug Facts

Active Ingredient

Avobenzone 3%,
Octisalate 5%,
Octocrylene 7%

Purpose

Sunscreen

Uses

- Helps prevent sunburn.
- if used as directed with other sun protection measures (see Directions), decreases the risk of skin cancer and early skin aging caused by the sun

Warnings

For external use only. Do not use ■ on damaged or broken skin. When using this product ■keep out of eyes. Rinse with water to remove. Stop use and ask a doctor if■ rash occurs.

Keep out of reach of children.If product is swallowed, get medical help or contact a Poison Control Center right away.

Directions

- Apply liberally 15 minutes before sun exposure
- Reapply at least every 2 hours.
- Use a water resistant sunscreen if swimming or sweating.
- Sun protection measures. Spending time in the sun increases your risk of cancer and early skin aging. To decrease this risk, regularly use a sunscreen with a Broad Spectrum SPF value of 15 or higher and other sun protection measures including:
  - Limit time in the sun, especially 10am - 2pm
  - Wear long-sleeved shirts, pants, hats and sun glasses.
  - Children under 6 months; Ask a doctor.

Other Information

- Protect this product from excessive heat and direct sun.
- May stain some fabrics.

Inactive Ingredients

Water, Isopropyl Lauroyl Sarcosinate, Glycerin, Dimethicone, Diisopropyl Sebacate, Sucrose Tristearate, Polymethyl Methacrylate, Silica, Aluminum Starch Octenylsuccinate, Pentylene Glycol, Polysorbate 61, Sodium Stearoyl Glutamate, Phenoxyethanol, Caprylyl Glycol, Tocopheryl Acetate, Dimethiconol, Glycyrrhetinic Acid, Xanthan Gum, Potassium Sorbate, Disodium EDTA, Panthenol, Carbomer, Allantoin, Triethanolamine, Zinc Gluconate, Hydroxypalmitoyl Sphinganine

Questions?

1-800-950-4695

Distributed by Alchemee LLC
Santa Monica, CA 90401
Made in Canada of foreign and domestic components
Proactiv is a trademark of The Proactiv Company Sàrl.

PRINCIPAL DISPLAY PANEL - 45 ML Tube Box

proactiv®

CLEAR SKIN
SPF 30

Broad-spectrum
SPF30
sunscreen

1.5 FL OZ
45 ML